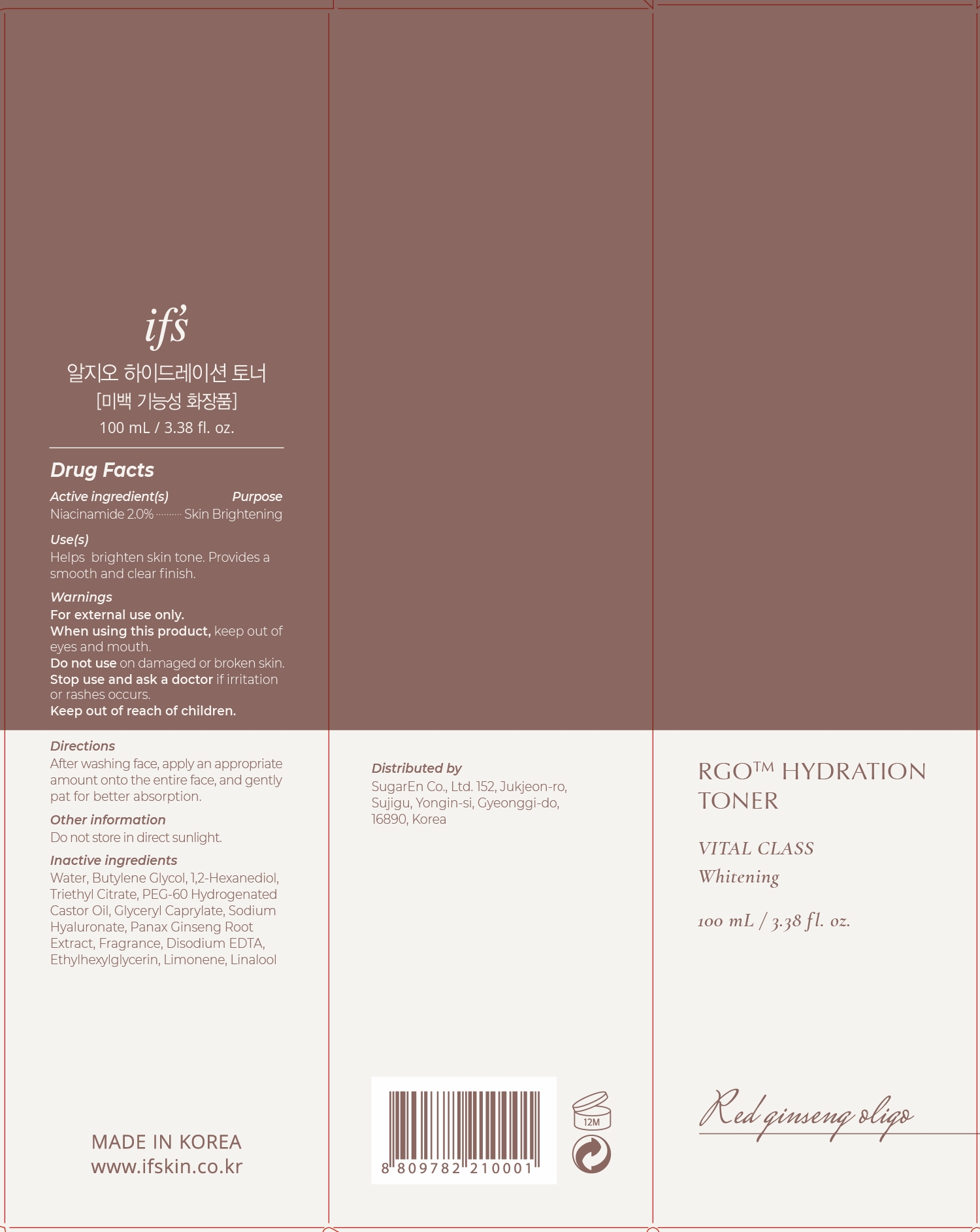 DRUG LABEL: RGO HYDRATION TONER
NDC: 81897-504 | Form: LIQUID
Manufacturer: SugarEn Co., Ltd.
Category: otc | Type: HUMAN OTC DRUG LABEL
Date: 20210530

ACTIVE INGREDIENTS: NIACINAMIDE 2 g/100 mL
INACTIVE INGREDIENTS: 1,2-HEXANEDIOL; POLYOXYL 60 HYDROGENATED CASTOR OIL; HYALURONATE SODIUM; LIMONENE, (+)-; LINALOOL, (+/-)-; TRIETHYL CITRATE; EDETATE DISODIUM ANHYDROUS; ETHYLHEXYLGLYCERIN; WATER; BUTYLENE GLYCOL; GLYCERYL CAPRYLATE; ASIAN GINSENG

81897-504 RGO HYDRATION TONER

Active ingredient(s)

Niacinamide 2.0%

Purpose

Skin Brightening

Use(s)

Helps brighten skin tone.

Provides an smooth and clear completion.

Warnings

For external only.

When using this product

keep out of eyes and mouth.

Do not use

on damaged or broken skin.

Stop use and ask a doctor

if irritation or rashes occurs.

Keep Out of reach of children

Other information

Do not store in direct sunlight.

Directions

After washing face, apply an appropriate amount onto the entire face, and gently pat for better absorption.

Inactive indredients

Water, Butylene Glycol, 1,2-Hexanediol, Triethyl Citrate, PEG-60 Hydrogenated Castor Oil, Glyceryl Caprylate, Sodium Hyaluronate, Panax Ginseng Root Extract, Fragrance, Disodium EDTA, Ethylhexylglycerin, Limonene, Linalool